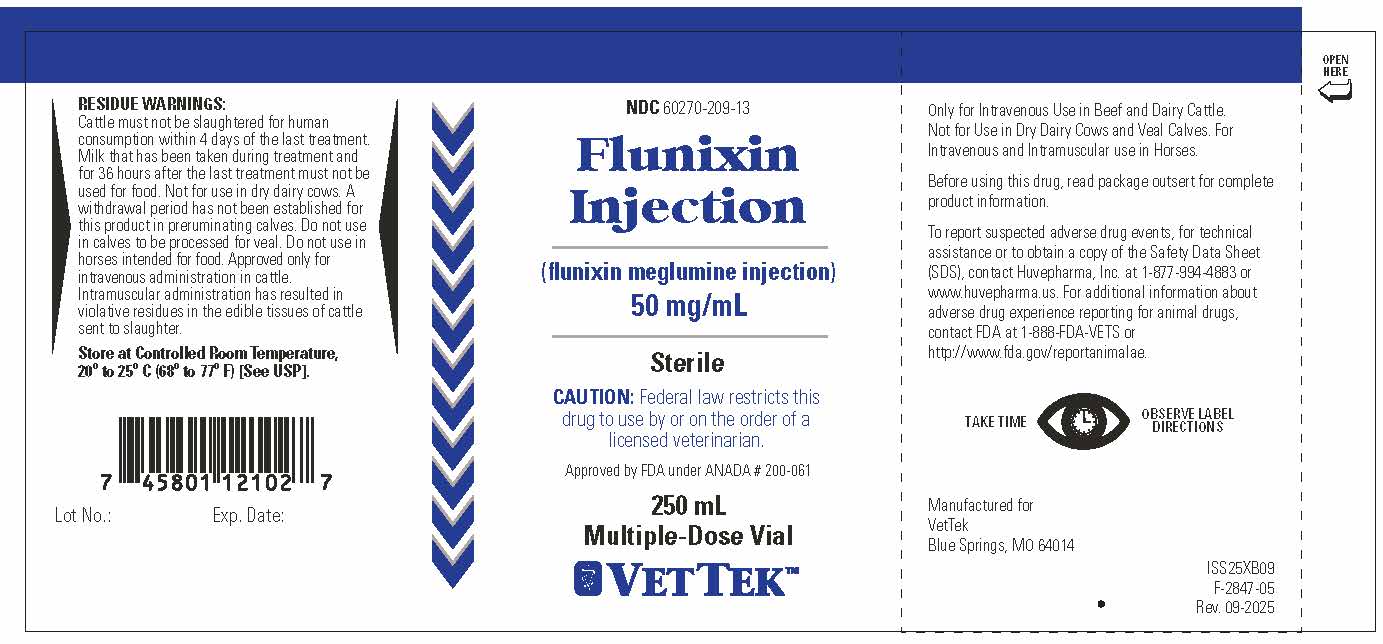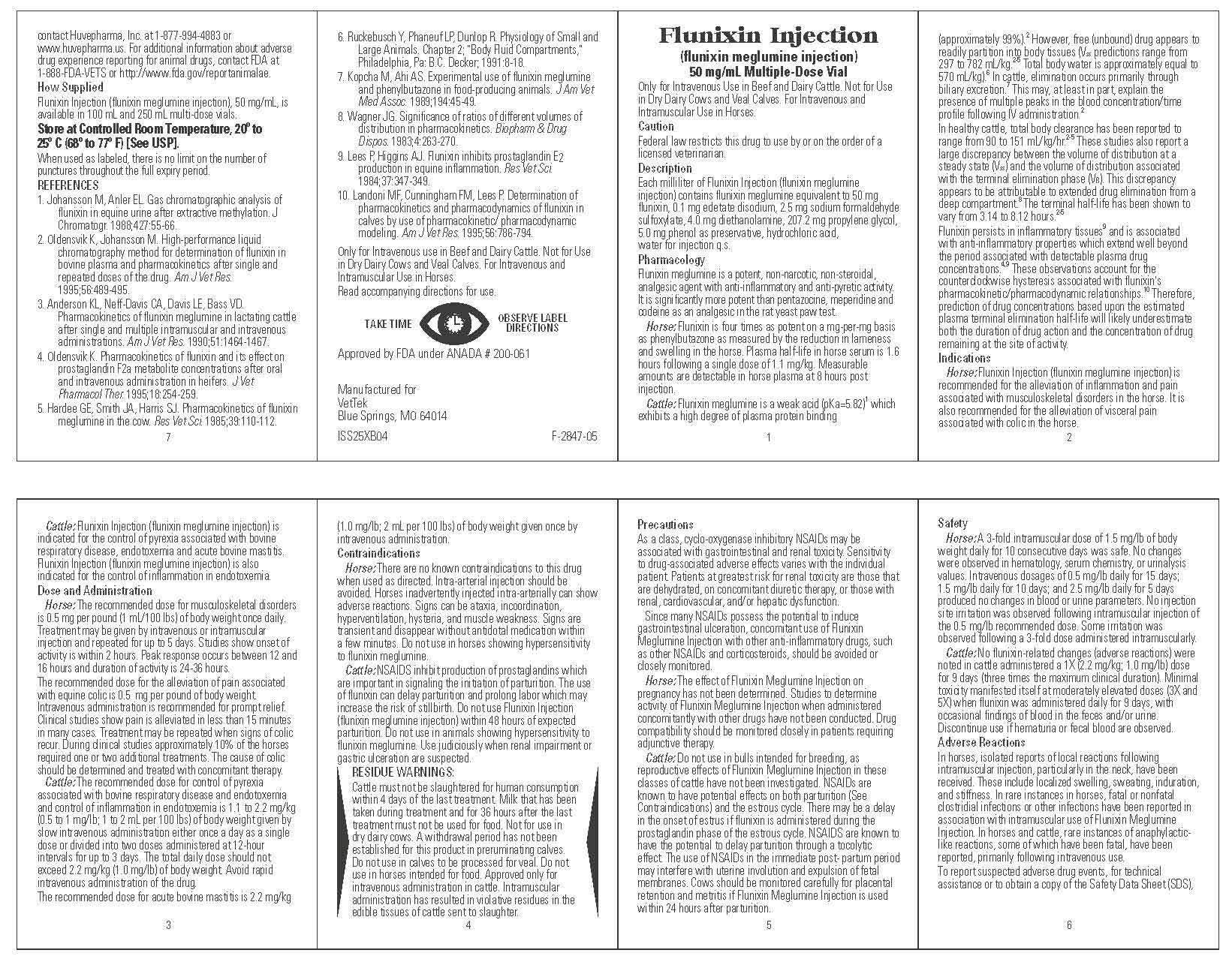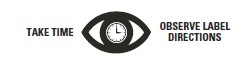 DRUG LABEL: Flunixin
NDC: 60270-209 | Form: INJECTION, SOLUTION
Manufacturer: VetTek
Category: animal | Type: PRESCRIPTION ANIMAL DRUG LABEL
Date: 20250513

ACTIVE INGREDIENTS: FLUNIXIN MEGLUMINE 50 mg/1 mL; PHENOL 5 mg/1 mL

WARNINGS AND PRECAUTIONS

NDC 60270-209-13

Flunixin Injection
(flunixin meglumine injection)
50 mg/mL

Sterile

GENERAL PRECAUTIONS

CAUTION: Federal law restricts this drug to use by or on the order of a licensed veterinarian.

Approved by FDA under ANADA # 200-061

250 mL
Multiple-Dose Vial

VETERINARY INDICATIONS

Only for Intravenous Use in Beef and Dairy Cattle.
Not for Use in Dry Dairy Cows and Veal Calves. For Intravenous and Intramuscular use in Horses.

Before using this drug, read package outsert for complete product information.

ADVERSE REACTIONS

To report suspected adverse drug events, for technical assistance or to obtain a copy of the Safety Data Sheet (SDS), contact Huvepharma, Inc. at 1-877-994-4883 or www.huvepharma.us. For additional information about adverse drug experience reporting for animal drugs, contact FDA at 1-888-FDA-VETS or http://www.fda.gov/reportanimalae.

Manufactured for
VetTek
Blue Springs, MO 64014

RESIDUE WARNINGS:
Cattle must not be slaughtered for human consumption within 4 days of the last treatment. Milk that has been taken during treatment and
for 36 hours after the last treatment must not be used for food. Not for use in dry dairy cows. A withdrawal period has not been established for
this product in preruminating calves. Do not use in calves to be processed for veal. Do not use in horses intended for food. Approved only for
intravenous administration in cattle. Intramuscular administration has resulted in violative residues in the edible tissues of cattle sent to slaughter.

STORAGE AND HANDLING

Store at Controlled Room Temperature,
20º to 25º C (68º to 77º F) [See USP].

Lot No.: Exp. Date:

Flunixin Injection
(flunixin meglumine injection)
50 mg/mL Multiple-Dose Vial

VETERINARY INDICATIONS

Only for Intravenous Use in Beef and Dairy Cattle. Not for Use in Dry Dairy Cows and Veal Calves. For Intravenous and Intramuscular Use in Horses.

GENERAL PRECAUTIONS

Caution
Federal law restricts this drug to use by or on the order of a licensed veterinarian.

Description
Each milliliter of Flunixin Injection (ﬂunixin meglumine injection) contains ﬂunixin meglumine equivalent to 50 mg ﬂunixin, 0.1 mg edetate disodium, 2.5 mg sodium formaldehyde sulfoxylate, 4.0 mg diethanolamine, 207.2 mg propylene glycol, 5.0 mg phenol as preservative, hydrochloric acid, water for injection q.s.

Pharmacology
Flunixin meglumine is a potent, non-narcotic, non-steroidal, analgesic agent with anti-inﬂammatory and anti-pyretic activity. It is signiﬁcantly more potent than pentazocine, meperidine and codeine as an analgesic in the rat yeast paw test.

Horse: Flunixin is four times as potent on a mg-per-mg basis as phenylbutazone as measured by the reduction in lameness and swelling in the horse. Plasma half-life in horse serum is 1.6 hours following a single dose of 1.1 mg/kg. Measurable amounts are detectable in horse plasma at 8 hours post injection.
Cattle: Flunixin meglumine is a weak acid (pKa=5.82)^1 which exhibits a high degree of plasma protein binding (approximately 99%).^2 However, free (unbound) drug appears to readily partition into body tissues (Vss predictions range from 297 to 782 mL/kg.^2-5 Total body water is approximately equal to 570 mL/kg).^6 In cattle, elimination occurs primarily through biliary excretion.^7 This may, at least in part, explain the presence of multiple peaks in the blood concentration/time proﬁle following IV administration.^2

In healthy cattle, total body clearance has been reported to range from 90 to 151 mL/kg/hr.^2-5 These studies also report a large discrepancy between the volume of distribution at a steady state (Vss) and the volume of distribution associated with the terminal elimination phase (Vß). This discrepancy appears to be attributable to extended drug elimination from a deep compartment.^8 The terminal half-life has been shown to vary from 3.14 to 8.12 hours.^2-5

Flunixin persists in inﬂammatory tissues^9 and is associated with anti-inﬂammatory properties which extend well beyond the period associated with detectable plasma drug concentrations.^4,9 These observations account for the counterclockwise hysteresis associated with ﬂunixin's pharmacokinetic/pharmacodynamic relationships.^10 Therefore, prediction of drug concentrations based upon the estimated plasma terminal elimination half-life will likely underestimate both the duration of drug action and the concentration of drug remaining at the site of activity.

Indications
Horse: Flunixin Injection (ﬂunixin meglumine injection) is recommended for the alleviation of inﬂammation and pain associated with musculoskeletal disorders in the horse. It is also recommended for the alleviation of visceral pain associated with colic in the horse.
Cattle: Flunixin Injection (ﬂunixin meglumine injection) is indicated for the control of pyrexia associated with bovine respiratory disease, endotoxemia and acute bovine mastitis. Flunixin Injection (ﬂunixin meglumine injection) is also indicated for the control of inﬂammation in endotoxemia.

Dose and Administration
Horse: The recommended dose for musculoskeletal disorders is 0.5 mg per pound (1 mL/100 lbs) of body weight once daily. Treatment may be given by intravenous or intramuscular injection and repeated for up to 5 days. Studies show onset of activity is within 2 hours. Peak response occurs between 12 and 16 hours and duration of activity is 24-36 hours.
The recommended dose for the alleviation of pain associated with equine colic is 0.5 mg per pound of body weight. Intravenous administration is recommended for prompt relief. Clinical studies show pain is alleviated in less than 15 minutes in many cases. Treatment may be repeated when signs of colic recur. During clinical studies approximately 10% of the horses required one or two additional treatments. The cause of colic should be determined and treated with concomitant therapy.
Cattle: The recommended dose for control of pyrexia associated with bovine respiratory disease and endotoxemia and control of inﬂammation in endotoxemia is 1.1 to 2.2 mg/kg (0.5 to 1 mg/lb; 1 to 2 mL per 100 lbs) of body weight given by slow intravenous administration either once a day as a single dose or divided into two doses administered at 12-hour intervals for up to 3 days. The total daily dose should not exceed 2.2 mg/kg (1.0 mg/lb) of body weight. Avoid rapid intravenous administration of the drug.
The recommended dose for acute bovine mastitis is 2.2 mg/kg 1.0 mg/lb; 2 mL per 100 lbs) of body weight given once by intravenous administration.

Contraindications
Horse: There are no known contraindications to this drug when used as directed. Intra-arterial injection should be avoided. Horses inadvertently injected intra-arterially can show adverse reactions. Signs can be ataxia, incoordination, hyperventilation, hysteria, and muscle weakness. Signs are transient and disappear without antidotal medication within a few minutes. Do not use in horses showing hypersensitivity to ﬂunixin meglumine.
Cattle: NSAIDS inhibit production of prostaglandins which are important in signaling the initiation of parturition. The use of ﬂunixin can delay parturition and prolong labor which may increase the risk of stillbirth. Do not use Flunixin Injection (ﬂunixin meglumine injection) within 48 hours of expected parturition. Do not use in animals showing hypersensitivity to ﬂunixin meglumine. Use judiciously when renal impairment or gastric ulceration are suspected.

RESIDUE WARNINGS:
Cattle must not be slaughtered for human consumption within 4 days of the last treatment. Milk that has been taken during treatment and
for 36 hours after the last treatment must not be used for food. Not for use in dry dairy cows. A withdrawal period has not been established for
this product in preruminating calves. Do not use in calves to be processed for veal. Do not use in horses intended for food. Approved only for
intravenous administration in cattle. Intramuscular administration has resulted in violative residues in the edible tissues of cattle sent to slaughter.

Precautions
As a class, cyclo-oxygenase inhibitory NSAIDs may be associated with gastrointestinal and renal toxicity. Sensitivity to drug-associated adverse effects varies with the individual patient. Patients at greatest risk for renal toxicity are those that are dehydrated, on concomitant diuretic therapy, or those with renal, cardiovascular, and/or hepatic dysfunction.

Since many NSAIDs possess the potential to induce gastrointestinal ulceration, concomitant use of Flunixin Meglumine Injection with other anti-inﬂammatory drugs, such as other NSAIDs and corticosteroids, should be avoided or closely monitored.

Horse: The effect of Flunixin Meglumine Injection on pregnancy has not been determined. Studies to determine activity of Flunixin Meglumine Injection when administered concomitantly with other drugs have not been conducted. Drug compatibility should be monitored closely in patients requiring adjunctive therapy.
Cattle: Do not use in bulls intended for breeding, as reproductive effects of Flunixin Meglumine Injection in these classes of cattle have not been investigated. NSAIDs are known to have potential effects on both parturition (See Contraindications) and the estrous cycle. There may be a delay in the onset of estrus if ﬂunixin is administered during the prostaglandin phase of the estrous cycle. NSAIDS are known to have the potential to delay parturition through a tocolytic effect. The use of NSAIDs in the immediate post-partum period may interfere with uterine involution and expulsion of fetal membranes. Cows should be monitored carefully for placental retention and metritis if Flunixin Meglumine Injection is used within 24 hours after parturition.

Safety
Horse: A 3-fold intramuscular dose of 1.5 mg/lb of body weight daily for 10 consecutive days was safe. No changes were observed in hematology, serum chemistry, or urinalysis values. Intravenous dosages of 0.5 mg/lb daily for 15 days; 1.5 mg/lb daily for 10 days; and 2.5 mg/lb daily for 5 days produced no changes in blood or urine parameters. No injection site irritation was observed following intramuscular injection of the 0.5 mg/lb recommended dose. Some irritation was observed following a 3-fold dose administered intramuscularly.
Cattle: No ﬂunixin-related changes (adverse reactions) were noted in cattle administered a 1X (2.2 mg/kg; 1.0 mg/lb) dose for 9 days (three times the maximum clinical duration). Minimal toxicity manifested itself at moderately elevated doses (3X and 5X) when ﬂunixin was administered daily for 9 days, with occasional ﬁndings of blood in the feces and/or urine. Discontinue use if hematuria or fecal blood are observed.

Adverse Reactions
In horses, isolated reports of local reactions following intramuscular injection, particularly in the neck, have been received. These include localized swelling, sweating, induration, and stiffness. In rare instances in horses, fatal or nonfatal clostridial infections or other infections have been reported in association with intramuscular use of Flunixin Meglumine Injection. In horses and cattle, rare instances of anaphylactic-like reactions, some of which have been fatal, have been reported, primarily following intravenous use.

To report suspected adverse drug events, for technical assistance or to obtain a copy of the Safety Data Sheet (SDS), contact Huvepharma, Inc. at 1-877-994-4883 or www.huvepharma.us. For additional information about adverse drug experience reporting for animal drugs, contact FDA at 1-888-FDA-VETS or http://www.fda.gov/reportanimalae.

How Supplied
Flunixin Injection (ﬂunixin meglumine injection), 50 mg/mL, is available in 100 mL and 250 mL multi-dose vials.

STORAGE AND HANDLING

Store at Controlled Room Temperature, 20º to 25º C (68º to 77º F) [See USP].
When used as labeled, there is no limit on the number of punctures throughout the full expiry period.

REFERENCES
1. Johansson M, Anler EL. Gas chromatographic analysis of
flunixin in equine urine after extractive methylation. J
Chromatogr. 1988;427:55-66.

2. Oldensvik K, Johansson M. High-performance liquid
chromatography method for determination of flunixin in
bovine plasma and pharmacokinetics after single and
repeated doses of the drug. Am J Vet Res.
1995;56:489-495.

3. Anderson KL, Neff-Davis CA, Davis LE, Bass VD.
Pharmacokinetics of flunixin meglumine in lactating cattle
after single and multiple intramuscular and intravenous
administrations. Am J Vet Res. 1990;51:1464-1467.

4. Oldensvik K. Pharmacokinetics of flunixin and its effect on
prostaglandin F2a metabolite concentrations after oral
and intravenous administration in heifers. J Vet
Pharmacol Ther. 1995;18:254-259.

5. Hardee GE, Smith JA, Harris SJ. Pharmacokinetics of flunixin
meglumine in the cow. Res Vet Sci. 1985;39:110-112.

6. Ruckebusch Y, Phaneuf LP, Dunlop R. Physiology of Small and
Large Animals. Chapter 2; "Body Fluid Compartments,"
Philadelphia, Pa: B.C. Decker; 1991:8-18.

7. Kopcha M, Ahi AS. Experimental use of flunixin meglumine
and phenylbutazone in food-producing animals. J Am Vet
Med Assoc. 1989;194:45-49.

8. Wagner JG. Significance of ratios of different volumes of
distribution in pharmacokinetics. Biopharm & Drug
Dispos. 1983;4:263-270.

9. Lees P, Higgins AJ. Flunixin inhibits prostaglandin E2
production in equine inflammation. Res Vet Sci.
1984;37:347-349.

10. Landoni MF, Cunningham FM, Lees P. Determination of
pharmacokinetics and pharmacodynamics of flunixin in
calves by use of pharmacokinetic/ pharmacodynamic
modeling. Am J Vet Res. 1995;56:786-794.

VETERINARY INDICATIONS

Only for Intravenous use in Beef and Dairy Cattle. Not for Use
in Dry Dairy Cows and Veal Calves. For Intravenous and
Intramuscular Use in Horses.
Read accompanying directions for use.

Approved by FDA under ANADA # 200-061

Manufactured for
VetTek
Blue Springs, MO 64014